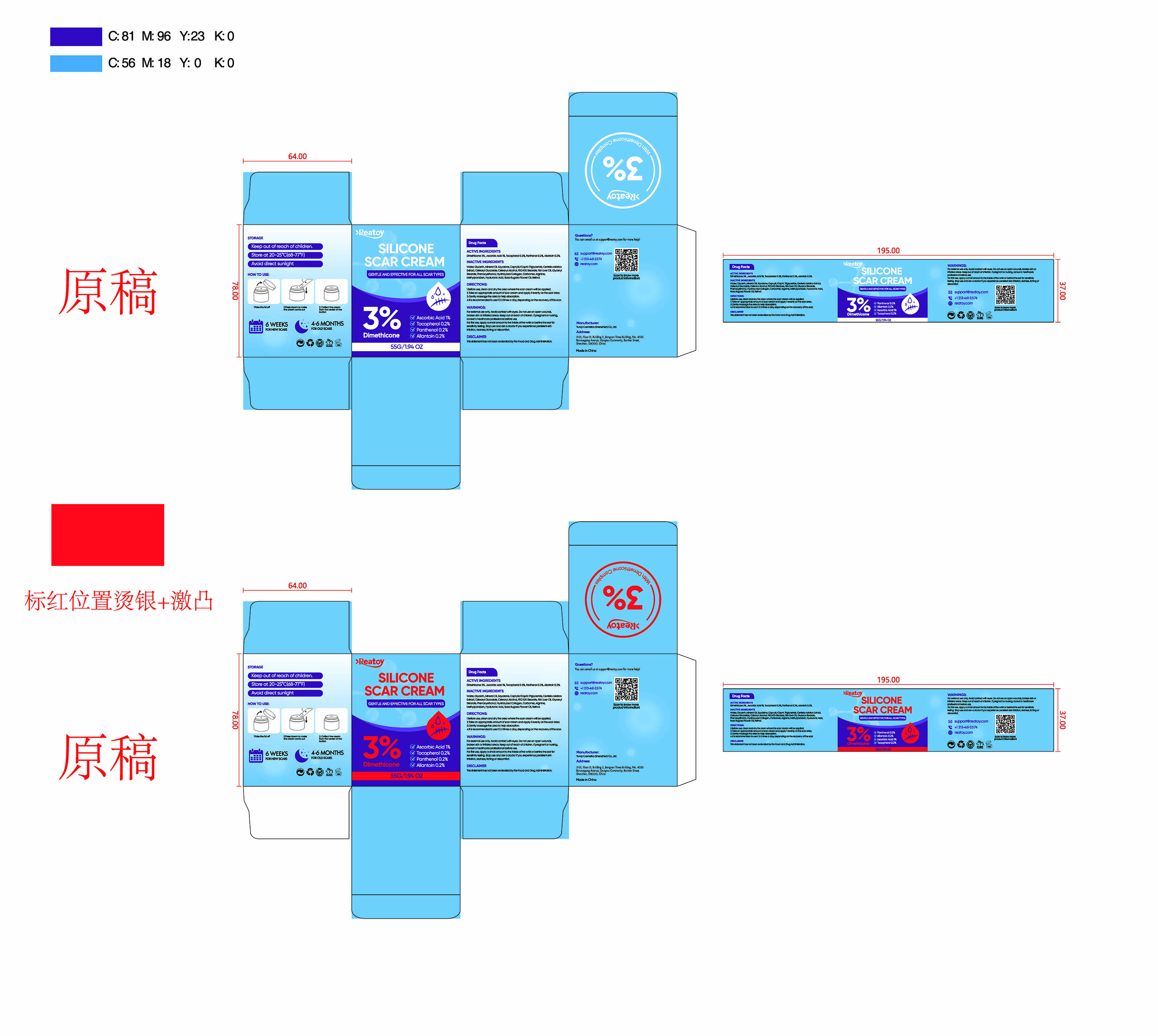 DRUG LABEL: SILICONE SCAR Cream
NDC: 84763-006 | Form: CREAM
Manufacturer: Yunqi Cosmetics (Shenzhen) Co., Ltd
Category: otc | Type: HUMAN OTC DRUG LABEL
Date: 20250424

ACTIVE INGREDIENTS: DIMETHICONE 0.03 g/1 g; ASCORBIC ACID 0.01 g/1 g; ALLANTOIN 0.002 g/1 g; TOCOPHEROL 0.002 g/1 g; PANTHENOL 0.002 g/1 g
INACTIVE INGREDIENTS: CARBOMER; ARGININE; CETEARYL GLUCOSIDE; MINERAL OIL; SQUALANE; CETEARYL ALCOHOL; PHENOXYETHANOL; GLYCERYL STEARATE; HYDROLYZED PORCINE COLLAGEN (ENZYMATIC; 3000 MW); METHYLPARABEN; CENTELLA ASIATICA TRITERPENOIDS; RETINOL; HYALURONIC ACID; ROSA RUGOSA FLOWER OIL; WATER; CAPRYLIC/CAPRIC TRIGLYCERIDE; PEG-100 STEARATE; GLYCERIN; FISH LIVER OIL

SILICONE SCAR CREAM

ACTIVE INGREDIENT

Dimethicone
Ascorbic Acid
Tocopherol
Panthenol
Allantoin

PURPOSE

SCAR CREAM

INDICATIONS AND USAGE

GENTLE AND EFFECTNE FOR ALL SCAR TYPES

WARNINGS

For exdemal use only

Do not use on open wounds broken skIn or lrttatedl areas.

WHEN USING

Avold contact wtth eves

Keep out of reach of chlldren

DOSAGE AND ADMINISTRATION

1.Before use, clean and dry the area where the scar cream will be applied.
2.Take an appropriate amount of scar cream and apply it evenly on the scar area.
3.Gemily massage the area to help absorplion.
4.t is recommencled to use it 2-3 times a day, depending on the recovery ofthe scar.

INACTIVE INGREDIENT

Water
Glycerin
Mineral Oil
Squalane
Caprylic/Capric Triglyceride
Centella Asiatica Extract
Cetearyl Glucoside
Cetearyl Alcohol
PEG-100 Stearate
Fish Liver Oil
Glyceryl Stearate
Phenoxyethanol
Hydrolyzed Collagen
Carbomer
Arginine
Methylparaben
Hyaluronic Acid
Rosa Rugosa Flower Oil
Retinol